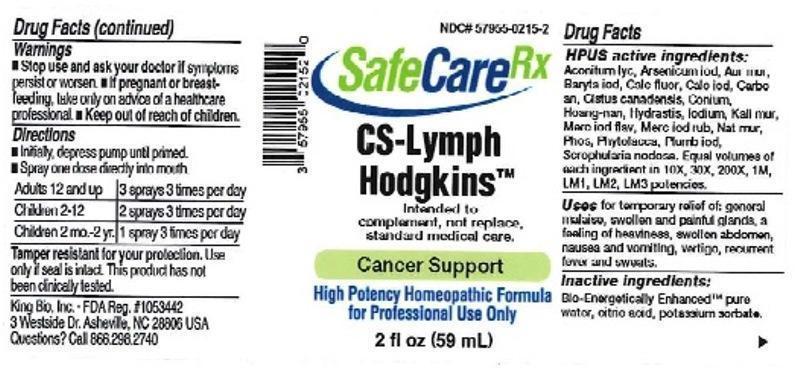 DRUG LABEL: CS Lymph Hodgkins
NDC: 57955-0215 | Form: LIQUID
Manufacturer: King Bio Inc.
Category: homeopathic | Type: HUMAN OTC DRUG LABEL
Date: 20160401

ACTIVE INGREDIENTS: ACONITUM LYCOCTONUM 10 [hp_X]/59 mL; ARSENIC TRIIODIDE 10 [hp_X]/59 mL; GOLD TRICHLORIDE 10 [hp_X]/59 mL; BARIUM IODIDE 10 [hp_X]/59 mL; CALCIUM FLUORIDE 10 [hp_X]/59 mL; CALCIUM IODIDE 10 [hp_X]/59 mL; CARBO ANIMALIS 10 [hp_X]/59 mL; HELIANTHEMUM CANADENSE 10 [hp_X]/59 mL; CONIUM MACULATUM FLOWERING TOP 10 [hp_X]/59 mL; STRYCHNOS WALLICHIANA BARK 10 [hp_X]/59 mL; GOLDENSEAL 10 [hp_X]/59 mL; IODINE 10 [hp_X]/59 mL; POTASSIUM CHLORIDE 10 [hp_X]/59 mL; MERCUROUS IODIDE 10 [hp_X]/59 mL; MERCURIC IODIDE 10 [hp_X]/59 mL; SODIUM CHLORIDE 10 [hp_X]/59 mL; PHOSPHORUS 10 [hp_X]/59 mL; PHYTOLACCA AMERICANA ROOT 10 [hp_X]/59 mL; LEAD IODIDE 10 [hp_X]/59 mL; SCROPHULARIA NODOSA 10 [hp_X]/59 mL
INACTIVE INGREDIENTS: WATER; ANHYDROUS CITRIC ACID; POTASSIUM SORBATE

CS Lymph Hodgkins™

ACTIVE INGREDIENT

Drug Facts__________________________________________________________________________________________________________

HPUS active ingredients: Aconitum lycoctonum, Arsenicum iodatum, Aurum muriaticum, Baryta iodata, Calcarea fluorica, Calcarea iodata, Carbo animalis, Cistus canadensis, Conium maculatum, Hoang-nan, Hydrastis canadensis, Iodium, Kali muriaticum, Mercurius iodatus flavus, Mercurius iodatus ruber, Natrum muriaticum, Phosphorus, Phytolacca decandra, Plumbum iodatum, Scrophularia nodosa. Equal volumes of each ingredient in 10X, 30X, 200X, 1M, LM1, LM2, LM3 potencies.

INDICATIONS AND USAGE

Uses for temporary relief of: general malaise, swollen and painful glands, a feeling of heaviness, swollen abdomen, nausea and vomiting, vertigo, recurrent fever and sweats.

Inactive Ingredients:

Bio-Energetically Enhanced™ pure water, citric acid and potassium sorbate.

Warnings

- Stop use and ask your doctor if symptoms persist or worsen.
- If pregnant or breast-feeding, take only on advice of a healthcare professional.

- Keep out of reach of children.

Directions

- Initially, depress pump until primed.
- Spray one dose directly into mouth.
- Adults 12 and up: 3 sprays 3 times per day.
- Children 2-12 years: 2 sprays 3 times per day.
- Children 2 mo-2 yr: 1 spray 3 times per day.

OTHER SAFETY INFORMATION

Tamper resistant for your protection. Use only if safety seal is intact. This product has not been clinically tested.

PURPOSE

Uses for temporary relief of:

- general malaise
- swollen and painful glands
- a feeling of heaviness
- swollen abdomen
- nausea and vomiting
- vertigo
- recurrent fever and sweats